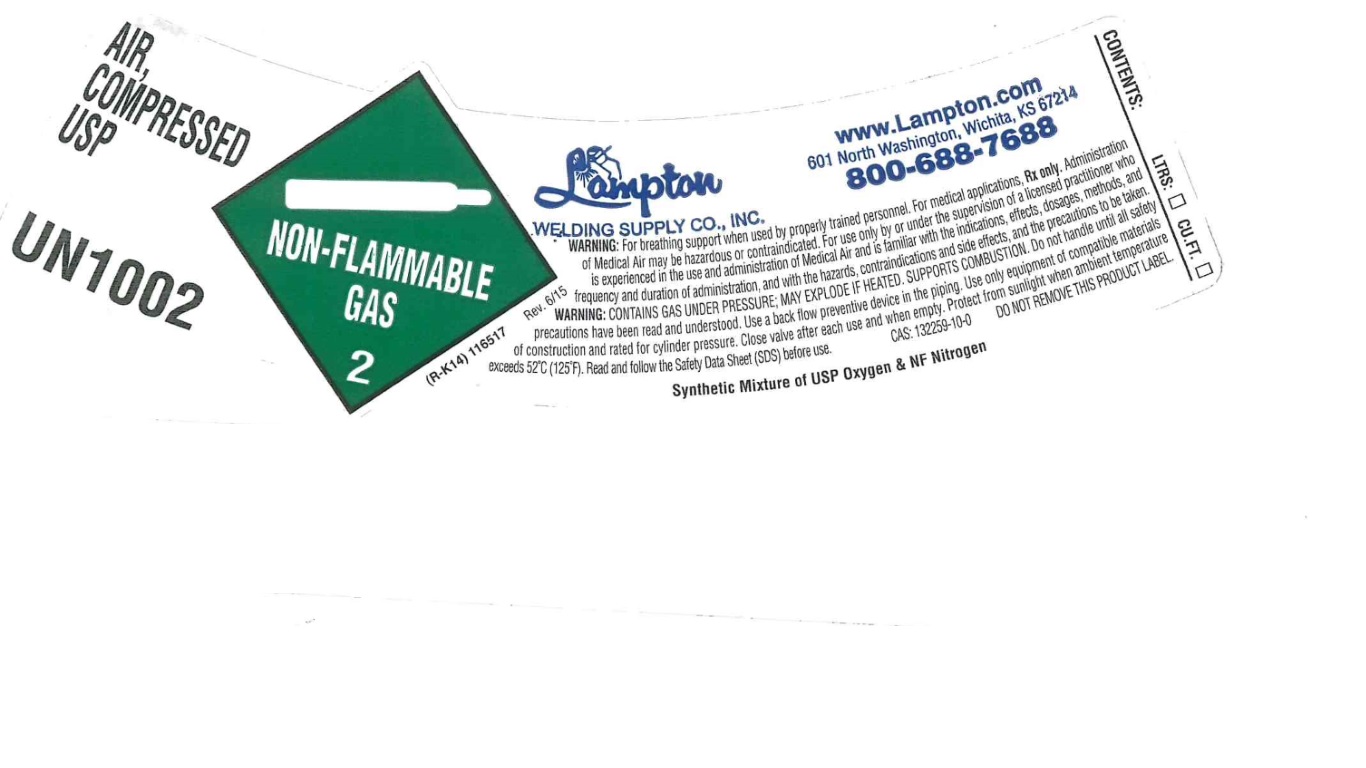 DRUG LABEL: Air
NDC: 58356-003 | Form: GAS
Manufacturer: Lampton Welding Supply Company, Inc
Category: prescription | Type: HUMAN PRESCRIPTION DRUG LABEL
Date: 20180418

ACTIVE INGREDIENTS: OXYGEN 21 L/1 L
INACTIVE INGREDIENTS: NITROGEN 79 L/1 L

Air

PACKAGE LABEL

AIR, COMPRESSED USP
UN1002
Lampton Welding Supply Co., Inc.
www.Lampton.com
601 North Washington, Wichita, KS 67214
800-688-7688
WARNING: For breathing support when used by properly trained personnel. For medical applications, Rx only. Administration of Medical Air may be hazardous or contraindicated. For use only by or under the supervision of a licensed practitioner who is experienced in the use and administration of Medical Air and is familiar with the indications, effects, dosages, methods, and frequency and duration of administration, and with the hazards, contraindications and side effects, and the precautions to be taken. WARNING: CONTAINS GAS UNDER PRESSURE; MAY EXPLODE IF HEATED. SUPPORTS COMBUSTION. Do not handle until all safety precautions have been read and understood. Use a back flow preventive device in the piping. Use only equipment of compatible materials of construction and rated for cylinder pressure. Close valve after each use and when empty. Protect from sunlight when ambient temperature exceeds 52 C (125 F). Read and follow the Safety Data Sheet (SDS) before use. CAS: 132259-10-0 DO NOT REMOVE THIS PRODUCT LABEL.
Synthetic Mixture of USP Oxygen & NF Nitrogen